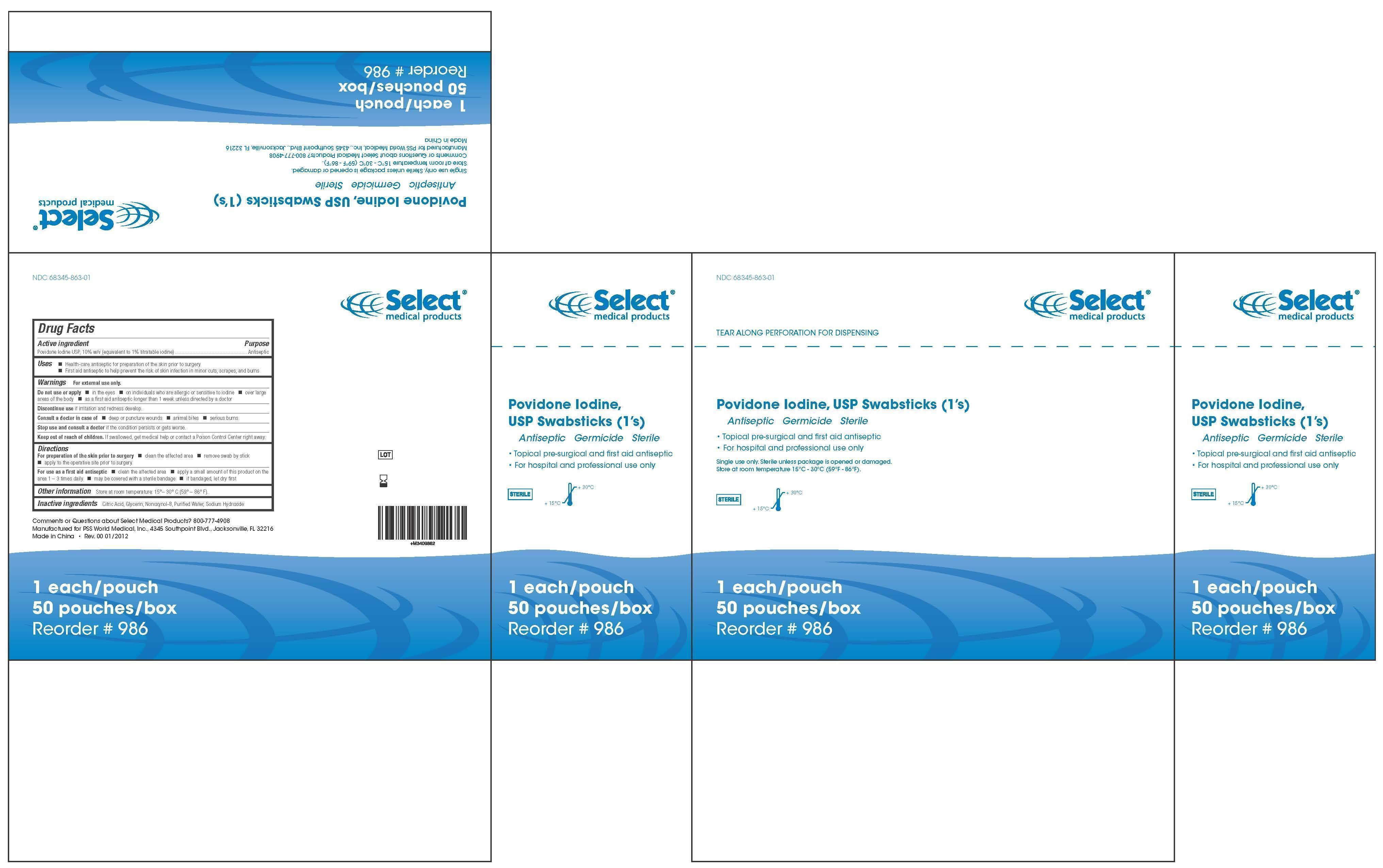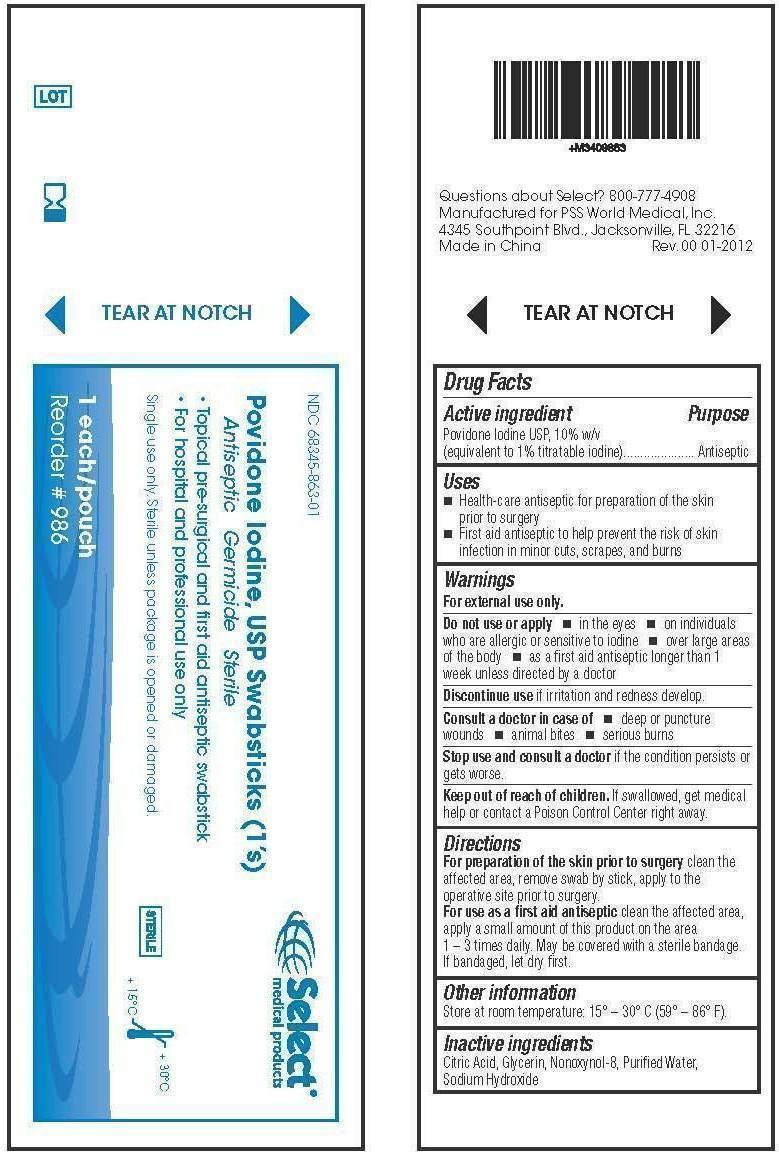 DRUG LABEL: Povidone Iodine
NDC: 68345-863 | Form: SWAB
Manufacturer: PSS World Medical, Inc.
Category: otc | Type: HUMAN OTC DRUG LABEL
Date: 20121002

ACTIVE INGREDIENTS: POVIDONE-IODINE 100 mg/1 mL
INACTIVE INGREDIENTS: CITRIC ACID MONOHYDRATE; GLYCERIN; NONOXYNOL-8; WATER; SODIUM HYDROXIDE

Povidone Iodine, USP Swabsticks

Active Ingredient

Povidone Iodine USP, 10% w/v

(equipvalent to 1% titratable iodine)

Purpose

Antiseptic

Uses

- Health-care antisptic for preparation of the skin prior to surgery
- First aid antiseptic to help prevent the risk of skin infection in minor cuts, scrapes, and burns

Warnings

For external use only.

Do not use or apply

- in the eyes
- on individuals who are allergic or sensitive to iodine
- over large areas of the body
- as a first aid antiseptic longer than 1 week unless directed by a doctor

Stop use and consult a doctor

Discontinue use if irritation and redness develop.

Consult a doctor in case of

- deep or puncture wounds
- animal bites
- serious burns

Stop use and cosult a doctor if the condition persists or gets worse.

Keep out of reach of children

If swallowed, get medical help or contact a Poison Control Center right away.

Directions

For preparation of the skin prior to surgery

Clean the affected area, remove swab by stick, apply to the operative site prior to surgery.

For use as a first aid antiseptic

Clean the affected area, apply a small amount of this product on the area 1-3 times daily. May be covered with a sterile bandage. If bandaged, let dry first.

Other information

Store at room temperature: 15-30C (59-86F)

Inactive Ingredients

Citrict Acid, Glycerin, Nonoxynol-8, Purified Water, Sodium Hydroxide

Questions

Questions about Select? 800-777-4908

Manufactured for PSS World Medical, Inc.

4345 Southpoint Blvd., Jacksonville, FL 32216

Made in China

Package Label

986 Each

9986 Box

68345-863-01

1 each/pouch

50 pouches/box

68345-863-03

3 each/pouch

25 pouches/box

PPovidone Iodine, USP Swabsticks

AAntiseptic Germicide Sterile

- Topical pre-surgical and first aid antiseptic swabstick
- For hospital and professional use only

Single use only. Sterile unless package is opened or damaged.